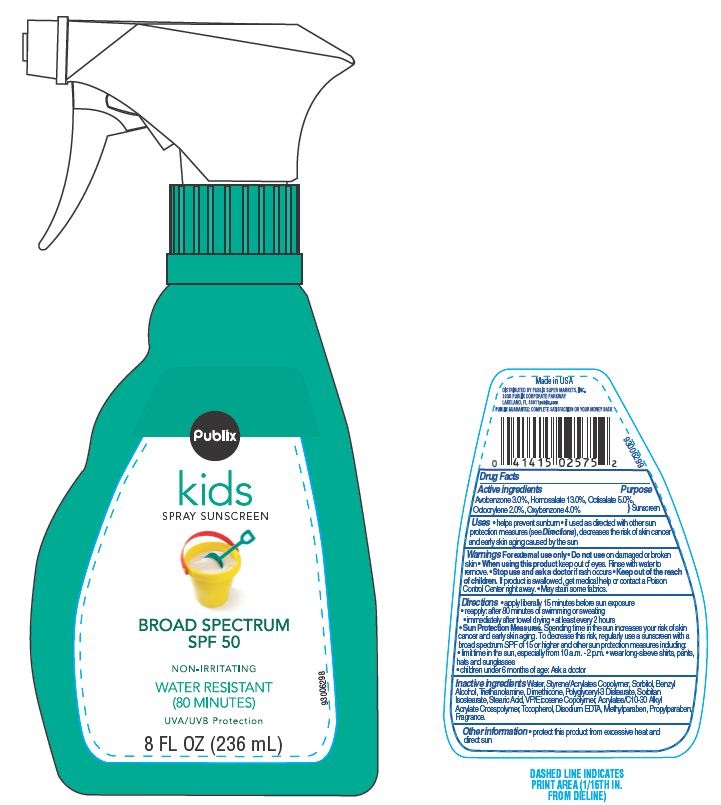 DRUG LABEL: Publix
NDC: 56062-706 | Form: SPRAY
Manufacturer: Publix Super Markets Inc
Category: otc | Type: HUMAN OTC DRUG LABEL
Date: 20130715

ACTIVE INGREDIENTS: AVOBENZONE 3 g/100 g; HOMOSALATE 13 g/100 g; OCTISALATE 5 g/100 g; OCTOCRYLENE 2 g/100 g; OXYBENZONE 4 g/100 g
INACTIVE INGREDIENTS: BENZYL ALCOHOL; SORBITAN ISOSTEARATE; DIMETHICONE; METHYLPARABEN; TOCOPHEROL; PROPYLPARABEN; EDETATE DISODIUM; WATER; SORBITOL; STEARIC ACID; TROLAMINE

Drug Facts

Active ingredients

Avobenzone 3.0%

Homosalate 13.0%

Octisalate 5.0%

Octocrylene 2.0%

Oxybenzone 4.0%

Purpose

Sunscreen

Uses

- helps prevent sunburn
- if used as directed with other sun protection measures (see Directions) decrease the risk of skin cancer and early skin aging caused by sun.

Warnings

For external use only

When using this product

- keep out of eyes. Rinse with water to remove.

Stop use and ask a doctor if

rash occurs

Keep out of the reach of children.

If swallowed get medical help or contact a Poison Control Center right away.

May stain some fabrics.

Directions

- apply literally 15 minutes before sun exposure
- reapply: after 80 minutes of swimming or sweating
- immediately after towel drying
- at least every 2 hours

Sun protection measures.

Spending time in the sun increase your risk of skin cancer and early skin

aging. To decrease this risk regularly use a sunscreen with a broad spectrum SPF of 15 or higher and other sun protection measures including:

- Limit time in the sun, especially from 10 am - 2 pm
- Wear long sleeves shirts, pants, hats and sunglasses
- children under 6 month of age: Ask a doctor

Other information

protect this product from excessive heat and direct sun

Inactive ingredients

Water, Styrene/Acrylates Copolymer, Sorbitol, Benzyl Alcohol, Triethanolamine, Dimethicone, Polyglyceryl-3 Distearate, Sorbitan Isostearate, Stearic Acid, VP/Eicosene Copolymer, Acrylates/C10-30 Alkyl Acrylate Crosspolymer, Tocopherol, Disodium EDTA, Methylparaben, Propylparaben, Fragrance.

Principal Display Panel

Publix

kids spray sunscreen

50 SPF

MOISTURIZING

VERY WATER RESISTANT

NON-IRRITATING

Broad Spectrum Protection

8 FL OZ(237 mL)